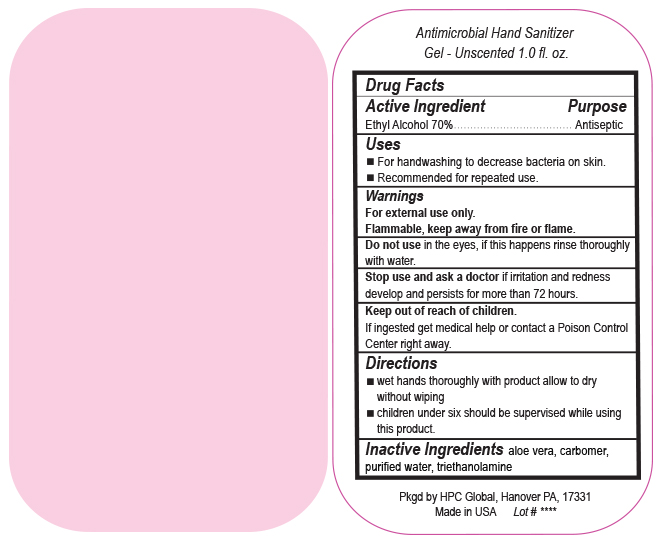 DRUG LABEL: Antimicrobial Hand Sanitizer Gel
NDC: 51811-726 | Form: GEL
Manufacturer: Hanover Pen Corp dba HPC Global
Category: otc | Type: HUMAN OTC DRUG LABEL
Date: 20200130

ACTIVE INGREDIENTS: ALCOHOL 20.699 mL/29.57 mL
INACTIVE INGREDIENTS: CARBOMER INTERPOLYMER TYPE A (ALLYL SUCROSE CROSSLINKED); ALOE VERA LEAF; WATER; TROLAMINE

Antimicrobial Hand Sanitizer Gel
alcohol gel

Antimicrobial Hand Sanitizer

Gel - Unscented 1.0 fl. oz.

Active Ingredient

Ehtyl Alcohol 70%

Purpose

Antiseptic

Uses

- For handwashing to decrease bacteria on skin.
- Recommended for repeated use.

Warnings

For external use only.

Flammable, keep away from fire or flame.

Do not use in the eyes, if this happens rinse thoroughly with water.

Stop use and ask a doctor if irritation and redness develop and persists for more than 72 hours.

Keep out of reach of children.

If ingested get medical help or contact a Poison Control Center right away.

Directions

- wet hands thoroughly with product allow to dry without wiping.
- children under six should be supervised while using this product.

Inactive Ingredients

aloe vera, carbomer, purified water, triethanolamine

Pkgd by HPC Global, Hanover PA, 17331

Made in USA Lot# ****